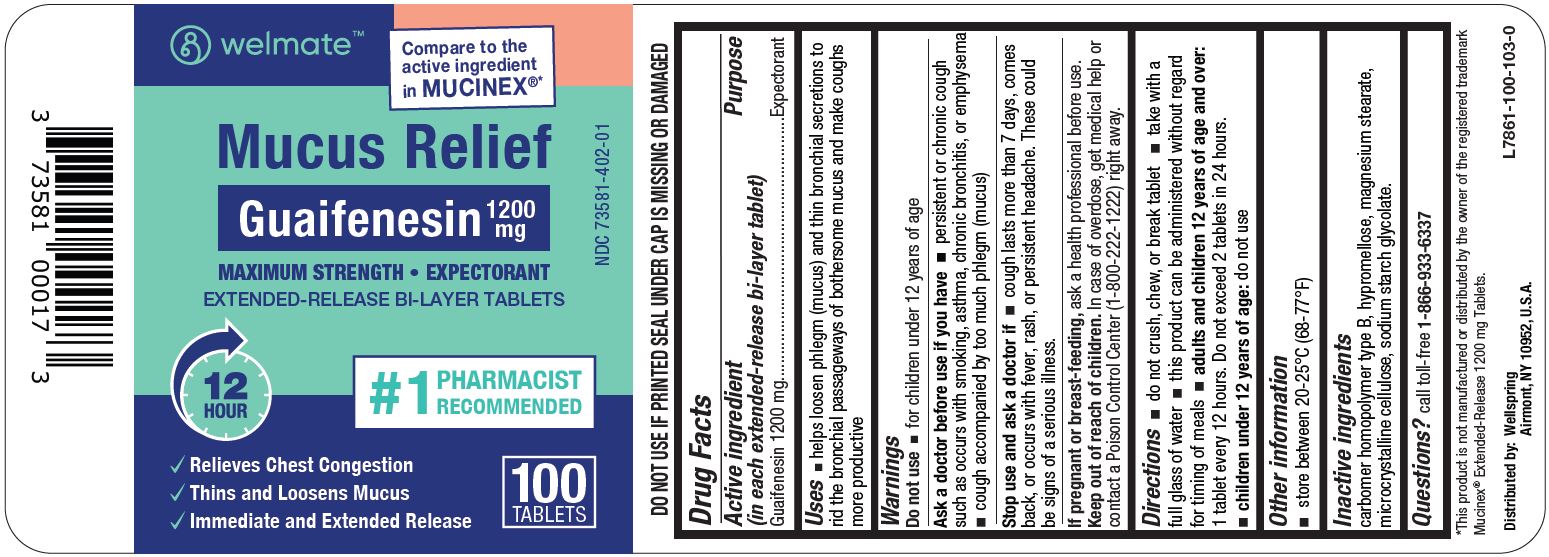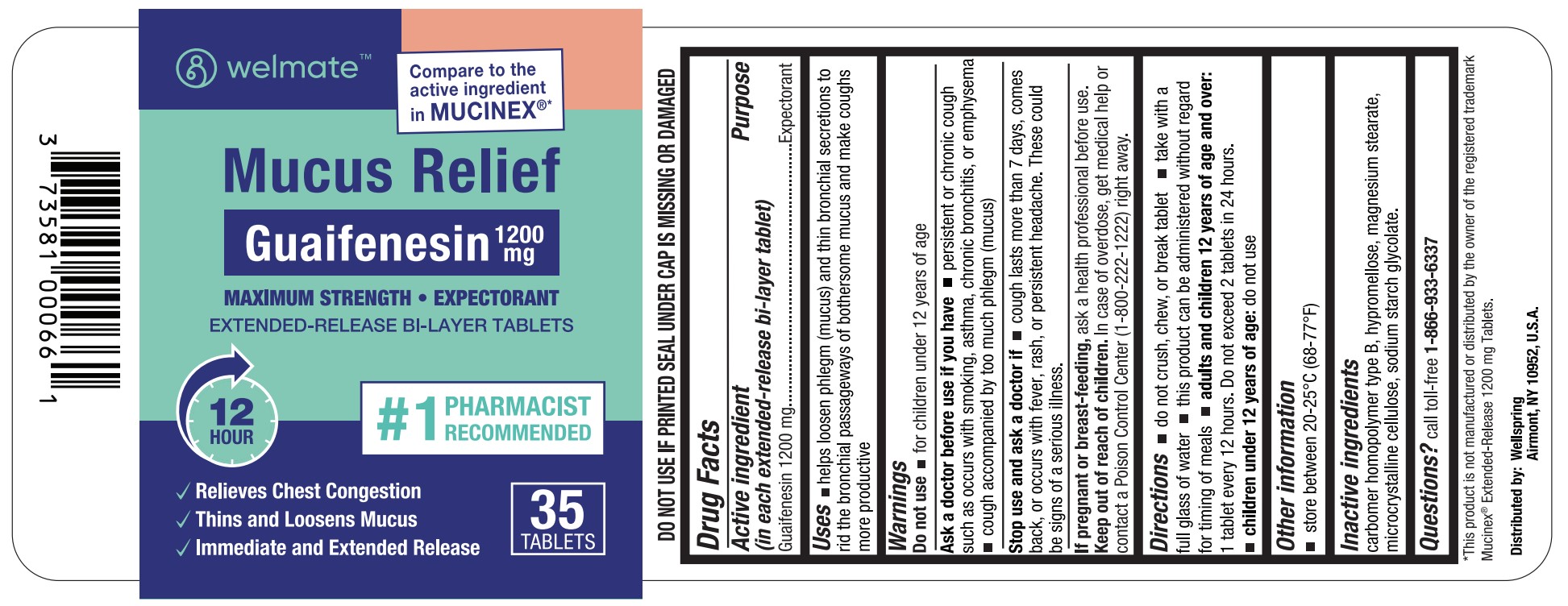 DRUG LABEL: MUCUS RELIEF
NDC: 73581-402 | Form: TABLET
Manufacturer: YYBA CORP
Category: otc | Type: HUMAN OTC DRUG LABEL
Date: 20251127

ACTIVE INGREDIENTS: GUAIFENESIN 1200 mg/1 1
INACTIVE INGREDIENTS: MAGNESIUM STEARATE; CARBOMER COPOLYMER TYPE B (ALLYL PENTAERYTHRITOL CROSSLINKED); HYPROMELLOSE, UNSPECIFIED; SODIUM STARCH GLYCOLATE TYPE A; MICROCRYSTALLINE CELLULOSE

YYBA (as PLD) - WELMATE - MUCUS RELIEF (GUAIFENESIN EXTENDED-RELEASE) TABLETS, 1200 MG (73581-402)

Active ingredient (in each extended-release bi-layer tablet)

GUAIFENESIN 1200 MG

PURPOSE

EXPECTORANT

Uses

- helps loosen phlegm (mucus) and thin bronchial secretions to rid the bronchial passageways of bothersome mucus and make coughs more productive

Warnings

Do not use

- for children under 12 years of age

Ask a doctor before use if you have

- persistent or chronic cough such as occurs with smoking, asthma, chronic bronchitis, or emphysema
- cough accompanied by too much phlegm (mucus)

Stop use and ask a doctor if

- cough lasts more than 7 days, comes back, or occurs with fever, rash, or persistent headache. These could be signs of a serious illness.

If pregnant or breast-feeding, ask a health professional before use.

Keep out of reach of children. In case of overdose, get medical help or contact a Poison Control Center (1-800-222-1222) right away.

Directions

- do not crush, chew, or break tablet
- take with a full glass of water
- this product can be administered without regard for timing of meals
- adults and children 12 years of age and over: 1 tablet every 12 hours. Do not exceed 2 tablets in 24 hours.
- children under 12 years of age: do not use

Other information

- store between 20° to 25°C (68° to 77°F)

Inactive ingredients

carbomer homopolymer type B, hypromellose, magnesium stearate, microcrystalline cellulose, sodium starch glycolate.

Questions?

call toll-free 1-866-933-6337